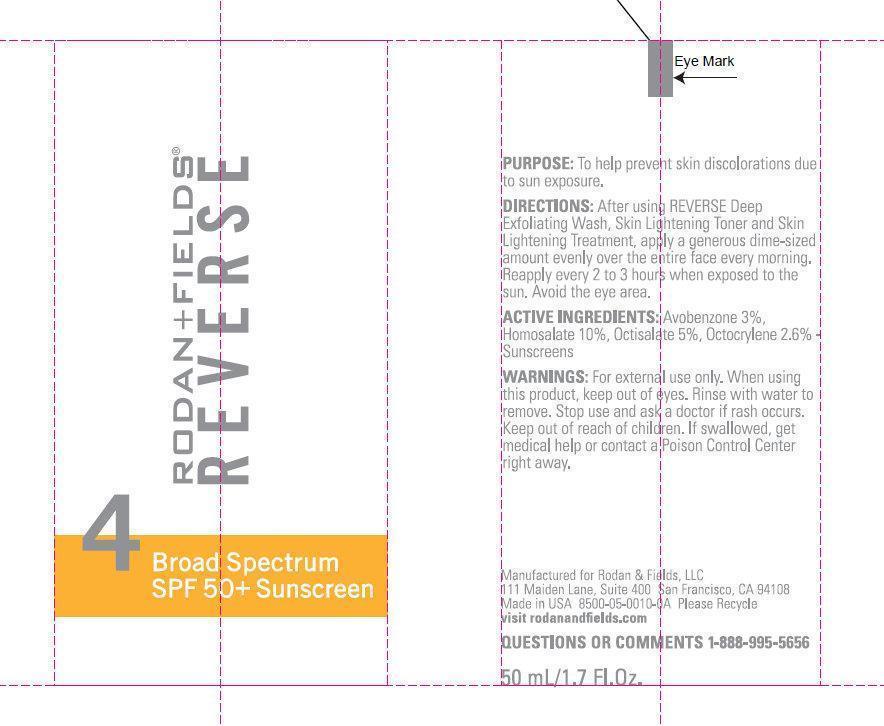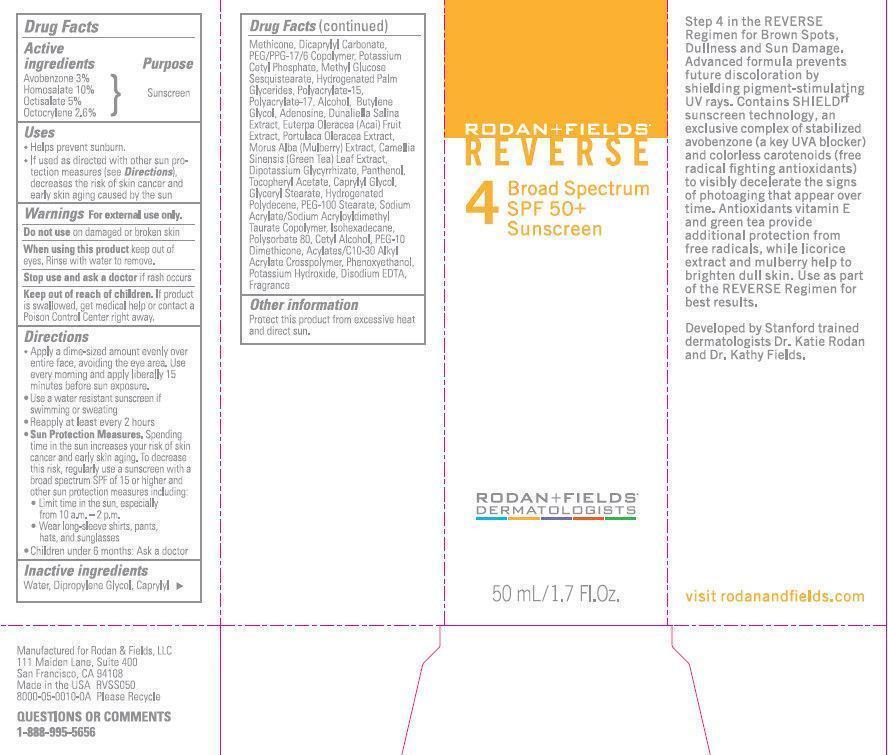 DRUG LABEL: RODAN AND FIELDS REVERSE 4 BROAD SPECTRUM SPF 50 PLUS SUNSCREEN
NDC: 14222-0420 | Form: CREAM
Manufacturer: Rodan & Fields
Category: otc | Type: HUMAN OTC DRUG LABEL
Date: 20260123

ACTIVE INGREDIENTS: AVOBENZONE 30 mg/1 mL; HOMOSALATE 100 mg/1 mL; OCTISALATE 50 mg/1 mL; OCTOCRYLENE 26 mg/1 mL
INACTIVE INGREDIENTS: WATER; DIPROPYLENE GLYCOL; CAPRYLYL TRISILOXANE; DICAPRYLYL CARBONATE; PEG/PPG-17/6 COPOLYMER; POTASSIUM CETYL PHOSPHATE; HYDROGENATED PALM GLYCERIDES; ALCOHOL; BUTYLENE GLYCOL; ADENOSINE; DUNALIELLA SALINA; ACAI; PURSLANE; WHITE MULBERRY; GREEN TEA LEAF; GLYCYRRHIZINATE DIPOTASSIUM; PANTHENOL; .ALPHA.-TOCOPHEROL ACETATE; CAPRYLYL GLYCOL; GLYCERYL MONOSTEARATE; PEG-100 STEARATE; ISOHEXADECANE; POLYSORBATE 80; CETYL ALCOHOL; PHENOXYETHANOL; POTASSIUM HYDROXIDE; EDETATE DISODIUM

RODAN AND FIELDS REVERSE 4 BROAD SPECTRUM SPF 50+ SUNSCREEN

Active ingredients

Avobenzone 3 % Homosalate 10% Octisalate 5% Octocrylene 2.6%

Purpose

Sunscreen

Uses

- Helps prevent sunburn.
- If used as directed with other sun protection measures (see), decreases the risk of skin cancer and early skin aging caused by the sun Directions

Warnings

For external use only.

Do not use

on damaged or broken skin

When using this product

keep out of eyes. Rinse with water to remove.

Stop use and ask a doctor

if rash occurs

Keep out of reach of children.

If product is swallowed, get medical help or contact a Poison Control Center right away.

Directions

- Apply a dime-sized amount evenly over entire face, avoiding the eye area. Use every morning and apply liberally 15 minutes before sun exposure.
- Use a water resistant sunscreen if swimming or sweating
- Reapply at least every 2 hours
- Spending time in the sun increases your risk of skin cancer and early skin aging. To decrease this risk, regularly use a sunscreen with a broad spectrum SPF of 15 or higher and other sun protection measures including: Sun Protection Measures.
- Limit time in the sun, especially from 10 a.m. - 2 p.m.
- Wear long-sleeve shirts, pants, hats, and sunglasses
- Children under 6 months: Ask a doctor

Inactive ingredients

Water, Dipropylene Glycol, Caprylyl Methicone, Dicaprylyl Carbonate, PEG/PPG-17/6 Copolymer, Potassium Cetyl Phosphate, Methyl Glucose Sesquistearate, Hydrogenated Palm Glycerides, Polyacrylate-15, Polyacrylate-17, Alcohol, Butylene Glycol, Adenosine, Dunaliella Salina Extract, Euterpa Olearacea (Acai) Fruit Extract, Portulaca Olearacea Extract, Morus Alba (Mulberry) Extract, Camellia Sinensis (Green Tea) Leaf Extract, Dipotassium Glycyrrhizate, Panthenol, Tocopheryl Acetate, Caprylyl Glycol, Glyceryl Stearate, Hydrogenated Polydecene, PEG-100 Stearate, Sodium Acrylate/Sodium Acryloyldimethyl Taurate Copolymer, Isohexadecane, Polysorbate 80, Cetyl Alcohol, PEG-10 Dimethicone, Acrylates/C10-30 Alkyl Acrylate Crosspolymer, Phenoxyethanol, Potassium Hydroxide, Disodium EDTA, Fragrance

Other information

Protect this product from excessive heat and direct sun.

Step 4 in the REVERSE Regimen for Brown Spots, Dullness and Sun Damage. Advanced formula prevents future discoloration by shielding pigment-stimulating UV rays. Contains SHIELD sunscreen technology, an exclusive complex of stabilized avobenzone (a key UVA blocker) and colorless carotenoids (free radical fighting antioxidants) to visibly decelerate the signs of photoaging that appear over time. Antioxidants vitamin E and green tea provide additional protection from free radicals, while licorice extract and mulberry help to brighten dull skin. Use as part of the REVERSE Regimen for best results.rf

Developed by Stanford trained dermatologists Dr. Katie Rodan and Dr. Kathy Fields. visit rodanandfields.com Manufactured for Rodan and Fields, LLC 11 Maiden Lane, Suite 400, San Francisco, CA 94108. Made in the USA Please Recycle.

QUESTIONS OR COMMENTS

1-888-995-5656

PACKAGE LABEL

RODAN + FIELDS REVERSE 4 Broad Spectrum SPF 50+ Sunscreen RODAN + FIELDS DERMATOLOGISTS 50 mL / 1.7 Fl.Oz.